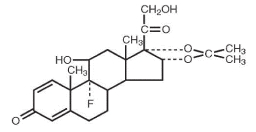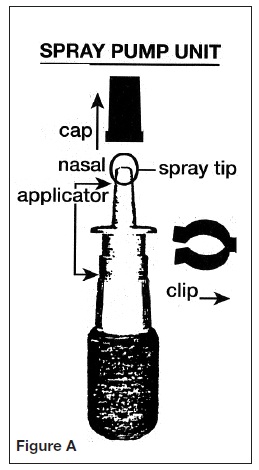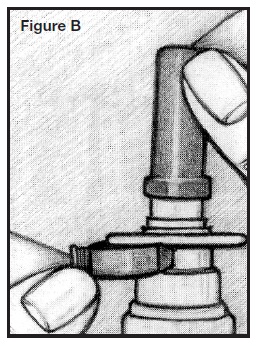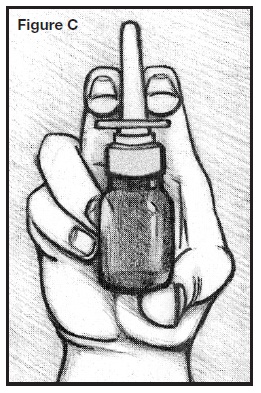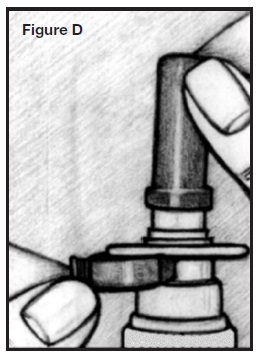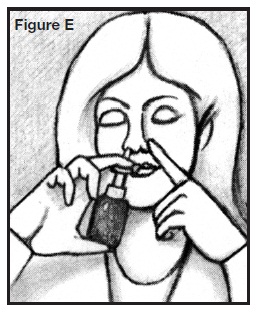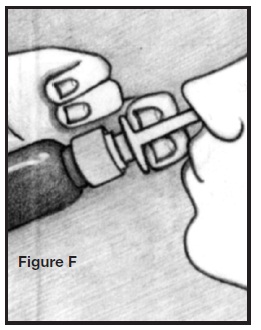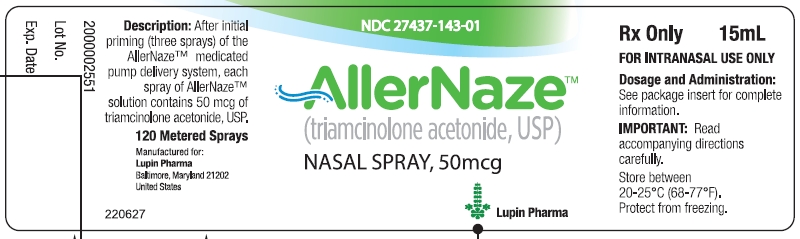 DRUG LABEL: AllerNaze
NDC: 27437-143 | Form: SPRAY, METERED
Manufacturer: Lupin Pharmaceuticals
Category: prescription | Type: HUMAN PRESCRIPTION DRUG LABEL
Date: 20101123

ACTIVE INGREDIENTS: TRIAMCINOLONE ACETONIDE 0.5 mg/1 mL
INACTIVE INGREDIENTS: CITRIC ACID MONOHYDRATE; EDETATE DISODIUM; POLYETHYLENE GLYCOL 3350; PROPYLENE GLYCOL; SODIUM CITRATE; BENZALKONIUM CHLORIDE; WATER

AllerNazeTM
(triamcinolone acetonide, USP)
nasal spray, 50 mcg

For Intranasal Use Only

DESCRIPTION:

Triamcinolone acetonide, the active ingredient of AllerNaze, is a corticosteroid with the chemical name, 9α-Fluoro-11β,16α, 17, 21-tetrahydroxypregna-1,4-diene-3, 20-dione cyclic 16, 17-acetal with acetone (C24 H31 FO6). Its structural formula is:

Triamcinolone acetonide, USP, is a white crystalline powder, with a molecular weight of 434.51. It is practically insoluble in water, and sparingly soluble in dehydrated alcohol, in chloroform and in methanol. It has a melting point temperature range between 292° and 294°C.

AllerNaze is a metered-dose manual spray pump in an amber polyethylene terephthalate (PET) bottle with 0.05% w/v triamcinolone acetonide in a solution containing citric acid, edetate disodium, polyethylene glycol 3350, propylene glycol, purified water, sodium citrate, and 0.01% benzalkonium chloride as a preservative. AllerNaze pH is 5.3.

After initial priming (three sprays) of the AllerNaze metered pump delivery system, each spray will deliver 50 mcg of triamcinolone acetonide. If the pump was not used for more than 14 days, reprime with 3 sprays or until a fine mist is observed. Each 15 mL bottle contains 7.5 mg of triamcinolone acetonide to deliver 120 metered sprays. After 120 sprays, the amount of triamcinolone acetonide delivered per spray may not be consistent and the bottle should be discarded.

CLINICAL PHARMACOLOGY:

Triamcinolone acetonide is a more potent derivative of triamcinolone. Triamcinolone acetonide is approximately eight times more potent than prednisone in animal models of inflammation. The clinical significance of this is unclear.

Although the precise mechanism of corticosteroid antiallergic action is unknown, corticosteroids have been shown to have a wide range of effects on multiple cell types (e.g. mast cells, eosinophils, neutrophils, macrophages, and lymphocytes) and mediators (e.g. histamines, eicosanoids, leukotrienes, and cytokines) involved in inflammation.

Pharmacokinetics:

Absorption:

The pharmacokinetics of triamcinolone acetonide solution was evaluated in a single-dose study conducted in 24 patients with perennial allergic rhinitis. Following a single intranasal dose of 400 mcg of triamcinolone acetonide (twice the recommended starting dose of triamcinolone acetonide solution), the mean C max of the drug was 1.12 ng/mL (SD = 0.38) with a median T max of 0.5 hours (range: 0.08 - 1.0).

A pharmacokinetic study to demonstrate dose proportionality was conducted in patients with perennial allergic rhinitis. The C max and AUC of the 200 and 400 mcg doses increased less than proportionally when compared to the 100 mcg dose. Following multiple dosing (100 or 200 or 400 mcg QD for 7 days), there was no evidence of drug accumulation.

Distribution:

The volume of distribution (Vd) reported was 99.5 L (SD = 27.5).

Metabolism:

In animal studies using rats and dogs, three metabolites of triamcinolone acetonide have been identified. They are 6β-hydroxytriamcinolone acetonide, 21-carboxytriamcinolone acetonide and 21-carboxy-6β-hydroxytriamcinolone acetonide. All three metabolites are expected to be substantially less active than the parent compound due to (a) the dependence of anti-inflammatory activity on the presence of a 21-hydroxyl group, (b) the decreased activity observed upon 6-hydroxylation, and (c) the markedly increased water solubility favoring rapid elimination. There appeared to be some quantitative differences in the metabolites among species. No differences were detected in metabolic pattern as a function of route of administration.

Elimination:

After a single intranasal dose of 400 mcg of triamcinolone acetonide (twice the recommended starting dose of triamcinolone acetonide solution), the mean observed elimination half-life was 2.26 hours (SD=0.77). Based upon intravenous dosing of triamcinolone acetonide phosphate ester, the half-life of triamcinolone acetonide was reported to be 88 minutes. The reported clearance was 45.2 L/hour (SD=9.1) for triamcinolone acetonide.

Special Populations

Age:

The effect of age, specifically in geriatric and pediatric patients, on the pharmacokinetics of triamcinolone acetonide has not been studied.

Gender:

Gender did not significantly influence the pharmacokinetics of triamcinolone acetonide solution.

Race:

The effect of race on the pharmacokinetics of triamcinolone acetonide solution has not been studied.

Renal/Hepatic Insufficiency:

No specific pharmacokinetic studies have been conducted in renally or hepatically impaired subjects.

Drug-Drug Interactions:

No specific drug-drug interactions have been investigated.

Pharmacodynamics:

A small (approximately 5 to 7 patients per treatment group), parallel trial was conducted to assess the effect of triamcinolone acetonide solution on the Hypothalamic-Pituitary-Adrenal (HPA) axis. Patients with allergic rhinitis were treated for six weeks with 400 mcg, 800 mcg, or 1600 mcg total daily doses of triamcinolone acetonide solution, 10 mg oral prednisone once daily, or placebo. Adrenal response to a six-hour cosyntropin stimulation test suggests that intranasal triamcinolone acetonide solution 400 mcg/day for six weeks did not measurably affect adrenal activity. Triamcinolone acetonide solution treatment arms using doses of 800 and 1600 mcg/day demonstrated a trend toward dose-related suppression of HPA response. However, this decrease did not reach statistical significance, whereas 10 mg daily oral prednisone did.

CLINICAL TRIALS:

The efficacy of triamcinolone acetonide solution has been evaluated in 746 patients with seasonal or perennial allergic rhinitis who completed 8 controlled clinical trials.

In total, 1187 patients have been treated with triamcinolone acetonide solution in the clinical development program. Three adequate and well controlled multi-center trials involving 541 patients with seasonal allergic rhinitis who received doses of triamcinolone acetonide solution ranging from 50 mcg to 400 mcg once daily were conducted. These trials evaluated the total nasal symptom scores that included stuffiness, rhinorrhea, itching, and sneezing.

The results showed that patients who received ≥ 200 mcg daily of the active drug had statistically significant relief in the total nasal symptom score compared to those receiving placebo.

In one clinical trial that examined efficacy after 2 days of 200 or 400 mcg triamcinolone acetonide solution treatment, only the 400 mcg dose showed statistically significant improvement over placebo in the nasal symptoms of seasonal allergic rhinitis.

INDICATIONS AND USAGE:

AllerNaze is indicated for the treatment of the nasal symptoms of seasonal and perennial allergic rhinitis in adults and children 12 years of age or older.

CONTRAINDICATIONS:

AllerNaze is contraindicated in patients with a hypersensitivity to any of its ingredients.

WARNINGS:

The replacement of a systemic corticosteroid with a topical corticosteroid can be accompanied by signs of adrenal insufficiency and, in addition, some patients may experience symptoms of corticosteroid withdrawal, e.g., joint or muscular pain, or both, lassitude and depression. Patients previously treated for prolonged periods with systemic corticosteroids and transferred to topical corticosteroids should be carefully monitored for acute adrenal insufficiency in response to stress. In those patients who have asthma or other clinical conditions which require long-term corticosteroid treatment, too rapid a decrease in systemic corticosteroid may cause a severe exacerbation of their symptoms.

Patients who are on immunosuppressant drugs are more susceptible to infections than healthy individuals. Chickenpox and measles, for example, can have a more serious or even fatal course in children or adults on immunosuppressant doses of corticosteroids. In children, or adults who have not had these diseases, particular care should be taken to avoid exposure. If exposed, therapy with varicella zoster immune globulin (VZIG) or pooled intravenous immunoglobulin (IVIG) as appropriate, may be indicated. If chickenpox develops, treatment with antiviral agents may be considered.

PRECAUTIONS:

General:

Intranasal corticosteroids may cause a reduction in growth velocity when administered to pediatric patients (see PRECAUTIONS, Pediatric Use section).

In clinical studies with triamcinolone acetonide nasal spray, the development of localized infections of the nose and pharynx with Candida albicans has rarely occurred. When such an infection develops it may require treatment with appropriate local therapy and discontinuance of treatment with AllerNaze.

AllerNaze should be used with caution, if at all, in patients with active or quiescent tuberculous infection of the respiratory tract or in patients with untreated fungal, bacterial, or systemic viral infections or ocular herpes simplex.

Because of the inhibitory effect of corticosteroids on wound healing, in patients who have experienced recent nasal septal ulcers, nasal surgery or trauma, a corticosteroid should be used with caution until healing has occurred. As with other nasally inhaled corticosteroids, nasal septal perforations have been reported in rare instances.

When used at excessive doses, systemic corticosteroid effects such as hypercorticism and adrenal suppression may appear. If such changes occur, AllerNaze should be discontinued slowly, consistent with accepted procedures for discontinuing oral corticosteroid therapy.

Systemic Availability and HPA Axis Suppression: Triamcinolone acetonide administered intranasally as triamcinolone acetonide solution has been shown to be absorbed into the systemic circulation in humans. The bioavailability of triamcinolone acetonide when administered as a solution in triamcinolone acetonide solution is approximately 5-fold greater than when administered as a CFC aerosol suspension formulation. While triamcinolone acetonide solution administered to 5 patients with allergic rhinitis at 400 mcg/day for 42 days did not measurably affect adrenal response to a six-hour cosyntropin stimulation test, the 6-hour cosyntropin test is an insensitive assessment for subtle HPA effects of corticosteroids. Doses of 800 and of 1600 mcg/day triamcinolone acetonide solution did demonstrate a trend toward dose-related suppression of the HPA response. However, this decrease did not reach statistical significance, whereas 10 mg daily oral prednisone did. (see Clinical Pharmacology, Pharmacodynamics)

INFORMATION FOR PATIENTS:

Patients being treated with AllerNaze should receive the following information and instructions:

- Patients who are on immunosuppressant doses of corticosteroids should be warned to avoid exposure to chickenpox or measles and, if exposed, to obtain medical advice.
- Patients should use AllerNaze at regular intervals since its effectiveness depends on its regular use. (See DOSAGE AND ADMINISTRATION)
- An improvement in some patient symptoms may be seen within the first two days of treatment, and generally, it takes one week of treatment to reach maximum benefit. Initial assessment for response should be made during this timeframe and periodically until the patient’s symptoms are stabilized.
- The patient should take the medication as directed and should not exceed the prescribed dosage. The patient should contact the physician if symptoms do not improve after three weeks, or if the condition worsens.
- Patients who experience recurrent episodes of epistaxis (nose bleeds) or nasal septum discomfort while taking this medication should contact their physician. Transient nasal irritation and/or burning or stinging may occur upon instillation with this product. Spraying triamcinolone acetonide directly into the eyes or onto the nasal septum should be avoided. For the proper use of this unit and to attain maximum improvement, the patient should read and follow the accompanying patient instructions carefully.
- The bottle should be discarded after 120 sprays following initial priming since the amount of triamcinolone acetonide delivered thereafter per spray may not be consistent. Do not transfer any remaining solution to another bottle.

CARCINOGENESIS, MUTAGENESIS AND IMPAIRMENT OF FERTILITY:

In two-year mouse and Sprague-Dawley rat studies, triamcinolone acetonide did not increase the incidence of tumors at oral doses up to 1 and 3 mcg/kg, respectively (less than the maximum recommended daily intranasal dose on a mcg/m^2 basis).

Triamcinolone acetonide has not been found to be mutagenic in Salmonella/mammalian-microsome reverse mutation assay (Ames test) or the chromosomal aberration test in the Chinese Hamster Ovary Cells.

Triamcinolone acetonide did not impair fertility in Sprague-Dawley rats given oral doses up to 15 mcg/kg (less than the maximum recommended daily intranasal dose on a mcg/m^2 basis).

However, triamcinolone acetonide caused increased fetal resorptions and stillbirths and decreased pup weight and survival at 5 mcg/kg (less than the maximum recommended daily intranasal dose on a mcg/m^2 basis). These effects were not produced at 1 mcg/kg (less than the maximum recommended daily intranasal dose on a mcg/m^2 basis).

PREGNANCY:

Teratogenic Effects: Pregnancy Category C

Triamcinolone acetonide was teratogenic in rats, rabbits, and monkeys. In rats, triamcinolone acetonide was teratogenic at inhalation doses of 20 mcg/kg and above (approximately 7/10 of the maximum recommended daily intranasal dose in adults on a mcg/m² basis). In rabbits, triamcinolone acetonide was teratogenic at inhalation doses 20 mcg/kg and above (approximately 2 times the maximum recommended daily intranasal dose in adults on a mcg/m² basis). In monkeys, triamcinolone acetonide was teratogenic at an inhalation dose of 500 mcg/kg and above (approximately 37 times the maximum recommended daily intranasal dose in adults on a mcg/m² basis). Dose-related teratogenic effects in rats and rabbits included cleft palate, or internal hydrocephaly, or both and axial skeletal defects, whereas the effects observed in the monkey were cranial malformations.

There are no adequate and well-controlled studies in pregnant women. Triamcinolone acetonide, like other corticosteroids, should be used during pregnancy only if the potential benefits justify the potential risk to the fetus. Since their introduction, experience with oral corticosteroids in pharmacologic as opposed to physiologic doses suggests that rodents are more prone to teratogenic effects from corticosteroids than humans. In addition, because there is a natural increase in corticosteroid production during pregnancy, most women will require a lower exogenous corticosteroid dose and many will not need corticosteroid treatment during pregnancy.

Nonteratogenic Effects:

Hypoadrenalism may occur in infants born of mothers receiving corticosteroids during pregnancy. Such infants should be carefully observed.

NURSING MOTHERS:

It is not known whether triamcinolone acetonide is excreted in human breast milk. Because other corticosteroids are excreted in human milk, caution should be exercised when AllerNaze is administered to nursing women.

PEDIATRIC USE:

Safety and effectiveness in pediatric patients below the age of 12 years have not been established. Controlled clinical studies have shown that intranasal corticosteroids may cause a reduction in growth velocity in pediatric patients. This effect has been observed in the absence of laboratory evidence of hypothalamic-pituitary-adrenal (HPA) axis suppression, suggesting that growth velocity is a more sensitive indicator of systemic corticosteroid exposure in pediatric patients than some commonly used tests of HPA axis function. The long-term effects of this reduction in growth velocity associated with intranasal corticosteroids, including the impact on final adult height, are unknown. The potential for "catch up" growth following discontinuation of treatment with intranasal corticosteroids has not been adequately studied. The growth of pediatric patients receiving intranasal corticosteroids, including AllerNaze, should be monitored routinely (e.g. via stadiometry). The potential growth effects of prolonged treatment should be weighed against clinical benefits obtained and the availability of safe and effective noncorticosteroid treatment alternatives. To minimize the systemic effects of intranasal corticosteroids, including AllerNaze, each patient should be titrated to the lowest dose that effectively controls his/her symptoms.

GERIATRIC USE:

Clinical studies of AllerNaze did not include sufficient numbers of subjects aged 65 and over to determine whether they respond differently from younger subjects. Other reported clinical experience has not identified differences in responses between the elderly and younger patients. In general, dose selection for an elderly patient should be cautious, usually starting at the low end of the dosing range, reflecting the greater frequency of decreased hepatic, renal, or cardiac function, and of concomitant disease or other drug therapy.

ADVERSE REACTIONS:

In adequate, well-controlled and uncontrolled studies, 1187 patients have received triamcinolone acetonide solution. The adverse reactions summarized below, are based upon seven placebo controlled clinical trials of 2-6 weeks duration in 847 patients with seasonal or perennial allergic rhinitis (504 patients received 200 mcg or 400 mcg per day of triamcinolone acetonide solution and 343 patients received vehicle placebo). Adverse events reported by 2% or more of patients (regardless of relationship to treatment) who received triamcinolone acetonide solution 200 or 400 mcg once daily and that were more common with triamcinolone acetonide solution than with placebo are displayed in the table below. Overall, the incidence and nature of adverse events with triamcinolone acetonide solution 400 mcg was comparable to that seen with triamcinolone acetonide solution 200 mcg and with vehicle placebo.

ADVERSE EVENTS REPORTED AT A FREQUENCY OF 2% OR GREATER AND MORE COMMON AMONG PATIENTS TREATED WITH TRIAMCINOLONE ACETONIDE SOLUTION THAN PLACEBO REGARDLESS OF RELATIONSHIP TO TREATMENT
ADVERSE EVENTS | 200 mcg of triamcinolone acetonide once daily n = 204 | 400 mcg of triamcinolone acetonide once daily n = 300 | Combined (200 and 400 mcg) use of triamcinolone acetonide n = 504 | Vehicle Placebo n = 343
BODY AS A WHOLE
Headache | 51.0% | 44.3% | 47.0% | 41.1%
Back Pain | 7.8% | 4.7% | 6.0% | 3.5%
RESPIRATORY SYSTEM
Pharyngitis | 13.7% | 10.3% | 11.7% | 7.9%
Asthma | 5.4% | 4.3% | 4.8% | 2.9%
Cough Increased | 2.0% | 2.7% | 2.4% | 2.3%
DIGESTIVE SYSTEM
Dyspepsia | 4.9% | 2.7% | 3.6% | 2.0%
Nausea | 2.0% | 3.0% | 2.6% | 0.6%
Vomiting | 1.5% | 2.7% | 2.2% | 1.5%
SPECIAL SENSES
Taste Perversion | 7.8% | 5.0% | 6.2% | 2.9%
Conjunctivitis | 4.4% | 1.3% | 2.6% | 1.5%
MUSCULOSKELETAL SYSTEM
Myalgia | 2.5% | 3.3% | 3.0% | 2.6%

Adverse events reported by 2% or more of patients who received triamcinolone acetonide solution 200 or 400 mcg once daily and that were more common with placebo than with triamcinolone acetonide solution included: application site reaction (e.g. transient nasal burning and stinging), rhinitis, dysmenorrhea, pain (unspecified) and allergic reaction.

The adverse effects related to the irritation of nasal mucous membranes (i.e. application site reaction) did not usually interfere with treatment. In the controlled and uncontrolled studies, approximately 0.3% of patients discontinued because of irritation of nasal mucous membranes.

OVERDOSAGE:

Like any other nasally administered corticosteroid, acute overdosing is unlikely in view of the total amount of active ingredient present. In the event that the entire contents of the bottle were administered all at once, via oral or nasal application, clinically significant adverse events would likely not result. The patient may experience some gastrointestinal upset. Chronic overdosage with any corticosteroid may result in signs or symptoms of hypercorticism (see PRECAUTIONS).

DOSAGE AND ADMINISTRATION:

The recommended starting dose of AllerNaze for most patients is 200 mcg per day given as 2 sprays (approximately 50 mcg/spray) in each nostril once a day. The maximum dose should not exceed 400 mcg per day. If the 400 mcg dose is used, it may be given either as a once a day dosage (4 sprays in each nostril) or divided into two daily doses of two sprays/nostril twice a day.

The nasal spray pump must be primed before AllerNaze is used for the first time. To prime the pump, press down on the shoulder of the white nasal applicator using your forefinger and middle finger while supporting the base of the bottle with your thumb. Press down and release the pump until it sprays 3 times or until a fine mist is observed (see DIRECTIONS FOR USE).

Some patients may obtain relief of symptoms sooner when started on a 400 mcg per day dose of AllerNaze than with 200 mcg per day. Onset of significant relief of nasal symptoms was seen within two days after starting treatment at 400 mcg once daily. A starting dose of 400 mcg per day may be considered in patients when starting therapy with AllerNaze in cases where a faster onset of relief is desirable. Generally, maximum relief of symptoms may take several days or up to one week to occur.

After symptoms have been brought under control, patients should be titrated to the minimum effective dose to reduce the possibility of adverse effects.

If relief of symptoms is not achieved after 14-21 days of AllerNaze therapy given in an adequate dose, AllerNaze should be discontinued and alternative diagnosis and therapies considered.

AllerNaze is not recommended for use in persons under 12 years of age since its safety and effectiveness have not been established in this age group.

DIRECTION FOR USE:

Illustrated patient instructions for use accompany each package of AllerNaze.

HOW SUPPLIED:

Each 15 mL bottle of AllerNaze (NDC 27437-143-01) contains 7.5 mg (0.50 mg/mL) of triamcinolone acetonide, USP and is fitted with a meter pump with white nasal applicator, teal blue dust cover and teal blue locking clip sealed in a foil pouch. The unit delivers 120 metered actuations and comes with a patient's instructions for use leaflet. The bottle should be discarded when the labeled number of actuations has been reached even though the bottle is not completely empty.

Keep out of reach of children.

Store at controlled room temperature: 20°-25°C (68°-77°F). Protect from freezing.

Use AllerNaze within 2 months after opening of the protective foil pouch or before expiration date, whichever comes first.

Rx only

Lupin Pharma
Baltimore, MD 21202
Tel: 1-800-399-2561
www.lupinpharmaceuticals.com

AllerNazeTM [AL-er-nāz]

(triamcinolone acetonide, USP)

Nasal Spray

PATIENT’S INSTRUCTIONS FOR USE

INFORMATION FOR THE PATIENT

These instructions provide a summary of important information about AllerNaze. Please read it carefully before use. Ask your doctor or pharmacist if you have any additional questions.

What is AllerNaze?

AllerNaze is a prescription medicine called a corticosteroid used to treat seasonal and year-round allergies in adults and children age 12 and older. When AllerNaze is sprayed in your nose, this medicine helps lessen the symptoms of sneezing, runny nose, and nasal itching associated with nasal allergies.

Do not use AllerNaze if you

1. are pregnant or planning to become pregnant.

2. are breast feeding.

3. have had a reaction to triamcinolone acetonide or to any other nasal spray.

How do I use AllerNaze?

- Use AllerNaze on a regular schedule exactly as prescribed by your doctor
- Do not use more AllerNaze or take it more often than your doctor tells you. It usually takes several days to one week of regular use to feel the medicine working.
- Protect your eyes from the spray.
- If your symptoms do not improve, or if they become worse, contact your doctor.
- Do not stop taking AllerNaze without contacting your doctor.
- AllerNaze does not relieve the red and itchy eye symptoms that some people have with allergic rhinitis. Ask your doctor for advice on treatment.
- Tell your doctor if you have irritation, burning or stinging inside your nose that does not go away when using AllerNaze.
- You may have nosebleeds after using AllerNaze. If so, contact your doctor right away.

Call your doctor for medical advice about side effects. You may report side effects to FDA at 1-800-FDA-1088.

Patient Instructions for Use

Read these instructions carefully before use. The following instructions tell you how to prepare your AllerNaze spray pump so that it is ready for your use.

Open the foil pouch and remove the pump unit. See Figure A for a picture of the spray pump, the cap, and the safety clip.

Priming the Pump:

The pump needs to be primed before using it for the first time and then again if you have not used the spray for 2 weeks. You will prime the pump the same way each time.

1. Remove the blue plastic cap and the blue safety clip from the nasal applicator of the spray pump unit. See Figure B.

2. Prime the pump by holding the bottle with your thumb on the bottom and your index and middle fingers on top, on either side of the white nasal applicator. See Figure C.

3. Point the bottle up and away from your eyes. Press down on either side of the white nasal applicator using your forefinger and middle finger, while supporting the base of the bottle with your thumb.

4. Press down and release the pump several times until you get 3 sprays or until a fine mist is seen. A fine mist can only be made by a rapid and firm pumping action. See Figure C.

Using the spray correctly:

1. Gently blow your nose to clear it before using the medication.

2. Remove the blue plastic cap and the blue safety clip from the nasal applicator. See Figure D.

3. Prime the pump. See Figures A, B, and C in the “Priming the Pump” section.

4. Tilt your head backward slightly. Breathe out slowly.

5. Use a finger on your other hand to close your nostril on the side not receiving the medication. See Figure E.

6. Insert spray tip into one nostril, as shown in the illustration. Do not insert too far back. Do not spray AllerNaze directly onto the nasal tissue inside your nose; aim the spray to the back of your nose. See Figure F.

7. Breathe in through the nostril and while breathing in press the applicator once to release the spray. You will need to press firmly and rapidly. Breathe out through your mouth.

8. If the doctor has prescribed 2 sprays on each side, repeat Step 7 (above) in the same nostril and then switch to use the nasal spray in the other nostril.

9. Do not blow your nose for 15 minutes.

10. After use, wipe the spray bottle applicator off with a tissue and put the cap and safety clip back on to the bottle.

If your nasal passages are severely swollen, your doctor may recommend a decongestant nasal spray or nose drops for 3 or 4 days before using AllerNaze.

CLEANING the nasal applicator:

If the nasal applicator becomes blocked, and does not spray, remove it and allow it to soak in warm water for 10-15 minutes. Then rinse the applicator with clean warm water, allow it to air dry and put it back on the bottle. Do not try to unblock the applicator by inserting a pin or other sharp object. This could change the amount of medicine you spray and cause an overdose.

STORING and discarding AllerNaze:

- Store between 68º to 77º F (20º to 25º C).
- Do not freeze.
- Use AllerNaze within 2 months after opening the protective foil pouch or before the expiration date on the box or label, whichever comes first.
- After using 120 sprays of AllerNaze throw the bottle away – the dose may not be accurate.

Information about nasal symptoms of allergies (allergic rhinitis):

Allergic rhinitis is a condition that causes swelling and increased watery fluid in the nose and nasal passages. This can result in sneezing, runny nose, itching, and difficulty in breathing through the nose.

This response is caused by an allergy to pollen that comes from many types of plants including trees, grasses, and weeds. Allergic responses of this type may also be caused by mold spores, house dust mites, animal dander, and other substances.

Lupin Pharma
Baltimore, MD 21202
Tel: 1-800-399-2561
www.lupinpharmaceuticals.com 2000002549

PACKAGE/LABEL PRINCIPAL DISPLAY PANEL

NDC 27437-143-01

AllerNaze™

(triamcinolone acetonide, USP)

NASAL SPRAY, 50mcg

Lupin Pharma